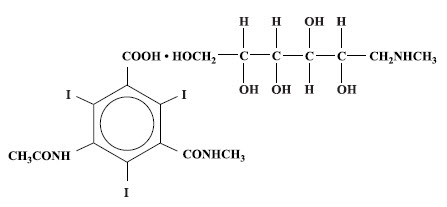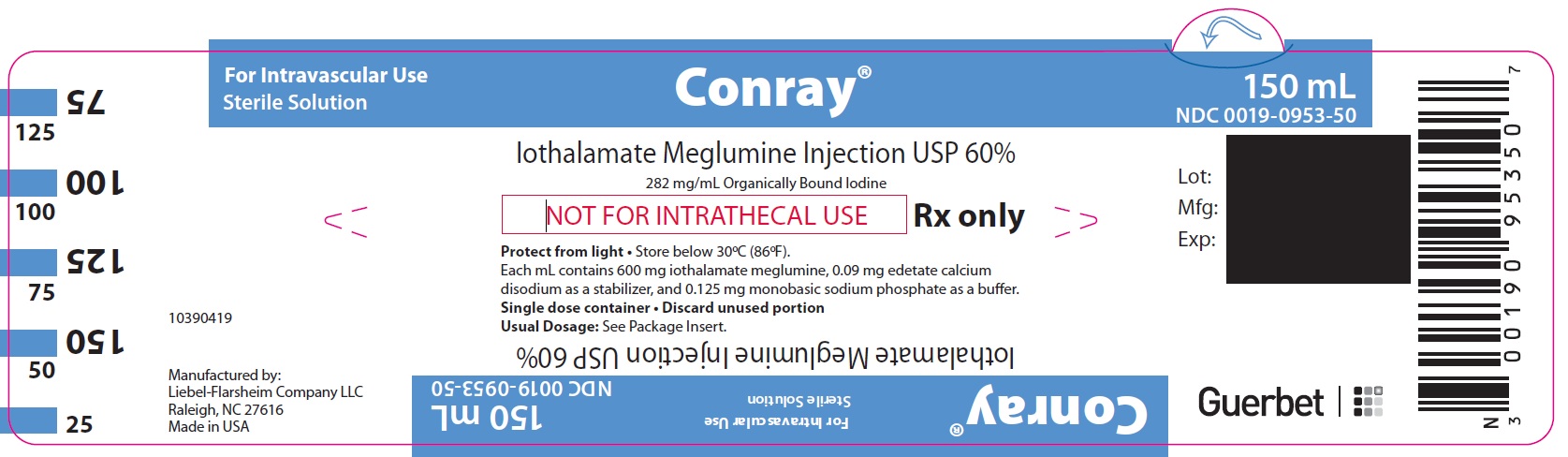 DRUG LABEL: Conray
NDC: 0019-0953 | Form: INJECTION
Manufacturer: Liebel-Flarsheim Company LLC
Category: prescription | Type: HUMAN PRESCRIPTION DRUG LABEL
Date: 20230511

ACTIVE INGREDIENTS: IOTHALAMATE MEGLUMINE 600 mg/1 mL
INACTIVE INGREDIENTS: EDETATE CALCIUM DISODIUM; SODIUM PHOSPHATE, MONOBASIC, UNSPECIFIED FORM

2/2023
Conray® (Iothalamate Meglumine Injection USP 60%)

BOXED WARNING

NOT FOR INTRATHECAL USE

DESCRIPTION

Conray is a sterile aqueous solution intended for use as a diagnostic radiopaque medium. Conray contains 60% w/v iothalamate meglumine, which is 1-deoxy-1-(methylamino)-D-glucitol 5-acetamido-2,4,6 triiodo-N-methylisophthalamate (salt), and has the following structural formula:

Each milliliter contains 600 mg of iothalamate meglumine, 0.09 mg edetate calcium disodium as a stabilizer and 0.125 mg of monobasic sodium phosphate as a buffer. The solution provides 28.2% (282 mg/mL) organically bound iodine. Conray has an osmolarity of approximately 1000 mOsmol per liter, an osmolality of approximately 1400 mOsmol per kilogram and is, therefore, hypertonic under conditions of use. The viscosity (cps) is approximately 6 at 25°C and 4 at 37°C. The pH is 6.5 to 7.7.

Conray is a clear solution containing no undissolved solids. Crystallization does not occur at normal room temperatures. It is supplied in containers from which the air has been displaced by nitrogen.

CLINICAL PHARMACOLOGY

Following intravascular injection, Conray is rapidly transported through the circulatory system to the kidneys and is excreted unchanged in the urine by glomerular filtration. The pharmacokinetics of intravascularly administered radiopaque contrast media are usually best described by a two compartment model with a rapid alpha phase for drug distribution and a slower beta phase for drug elimination. In patients with normal renal function, the alpha and beta half-lives of Conray were approximately 10 and 90 minutes, respectively.

Angiography may be performed following intravascular injection which will permit visualization until significant hemodilution occurs.

Renal accumulation is sufficiently rapid that maximum radiographic density in the calyces and pelves occurs, in most instances, about 3 to 8 minutes after injection. In patients with impaired renal function, diagnostic opacification frequently is achieved only after prolonged periods.

Injectable iodinated contrast agents are excreted either through the kidneys or through the liver. These two excretory pathways are not mutually exclusive, but the main route of excretion seems to be related to the affinity of the contrast medium for serum albumin. Iothalamate salts are poorly bound to serum albumin, and are excreted mainly through the kidneys.

The liver and small intestine provide the major alternate route of excretion. In patients with severe renal impairment, the excretion of this contrast medium through the gallbladder and into the small intestine sharply increases.

Iothalamate salts cross the placental barrier in humans and are excreted unchanged in human milk.

The biliary system, pancreatic duct or joint spaces may be visualized by the direct injection of contrast medium into the region to be studied.

CT Scanning of the Head

When used for contrast enhancement in computed tomographic brain scanning, the degree of enhancement is directly related to the amount of iodine administered. Rapid injection of the entire dose yields peak blood iodine concentrations immediately following the injection, which fall rapidly over the next five to ten minutes. This can be accounted for by the dilution in the vascular and extracellular fluid compartments which causes an initial sharp fall in plasma concentration. Equilibration with the extracellular compartments is reached by about ten minutes; thereafter, the fall becomes exponential. Maximum contrast enhancement frequently occurs after peak blood iodine levels are reached. The delay in maximum contrast enhancement can range from five to forty minutes, depending on the peak iodine levels achieved and the cell type of the lesion. This lag suggests that the contrast enhancement of the image is at least in part dependent on the accumulation of iodine within the lesion and outside the blood pool.

In brain scanning, the contrast medium (Conray) does not accumulate in normal brain tissue due to the presence of the “blood brain barrier.” The increase in x-ray absorption in the normal brain is due to the presence of the contrast agent within the blood pool. A break in the blood brain barrier, such as occurs in malignant tumors of the brain, allows accumulation of contrast medium within the interstitial tumor tissue; adjacent normal brain tissue does not contain the contrast medium.

The image enhancement of non-tumoral lesions, such as arteriovenous malformations and aneurysms, is dependent on the iodine content of the circulating blood pool.

When used for cranial computerized angiotomography, rapid bolus injection and/or infusion combined with rapid CT scanning will provide clear delineation of the cerebral vessels.

CT Scanning of the Body^1

In non-neural tissues (during CT of the body), Conray diffuses rapidly from the vascular to the extra-vascular space. Increase in x-ray absorption is related to blood flow, concentration of the contrast medium and extraction of the contrast medium by interstitial tissue, since no barrier exists; contrast enhancement is thus due to the relative differences in extra-vascular diffusion between normal and abnormal tissue, a situation quite different than that in the brain.

The pharmacokinetics of Conray in normal and abnormal tissues has been shown to be variable.

Enhancement of CT with Conray may be of benefit in establishing diagnoses of certain lesions in some sites with greater assurance than is possible with unenhanced CT and in supplying additional features of the lesions. In other cases, the contrast medium may allow visualization of lesions not seen with CT alone or may help to define suspicious lesions seen with unenhanced CT.

Contrast enhancement appears to be greatest within the 30 to 90 seconds after bolus administration of the contrast agent, and after intra-arterial, rather than intravenous, administration. Therefore, the use of a continuous scanning technique (a series of 2 to 3 second scans beginning at the injection - dynamic CT scanning) may improve enhancement and diagnostic assessment of tumors and other lesions, such as an abscess, occasionally revealing more extensive disease. A cyst, or similar non-vascularized lesion, may be distinguished from vascularized solid lesions by comparing enhanced and unenhanced scans; non-vascularized lesions show no change in CT number, whereas vascularized lesions would show an increase. The latter might be benign, malignant or normal, but it is unlikely that it would be a cyst, hematoma, or other non-vascularized lesion.

Because unenhanced scanning may provide adequate information in the individual patient, the decision to employ contrast enhancement, which is associated with additional risk and increased exposure, should be based upon a careful evaluation of clinical, other radiological, and unenhanced CT findings.

INDICATIONS AND USAGE

Conray is indicated for use in excretory urography, cerebral angiography, peripheral arteriography, venography, arthrography, direct cholangiography, endoscopic retrograde cholangiopancreatography, contrast enhancement of computed tomographic brain images, cranial computerized angiotomography, intravenous digital subtraction angiography and arterial digital subtraction angiography.

Conray may also be used for enhancement of computed tomographic scans performed for detection and evaluation of lesions in the liver, pancreas, kidneys, abdominal aorta, mediastinum, abdominal cavity and retroperitoneal space. Continuous or multiple scans separated by intervals of 1 to 3 seconds during the first 30 to 90 seconds post-injection of the contrast medium (dynamic CT scanning) may provide enhancement of diagnostic significance, and may be of benefit in establishing diagnoses of certain lesions in these sites with greater assurance than is possible with CT alone, and in supplying additional features of the lesions. In other cases, the contrast agent may allow visualization of lesions not seen with CT alone, or may help to define suspicious lesions seen with unenhanced CT (see CLINICAL PHARMACOLOGY). Subsets of patients in whom delayed body CT scans might be helpful have not been identified. Inconsistent results have been reported and abnormal and normal tissues may be isodense during the time frame used for delayed CT scanning. The risks of such indiscriminate use of contrast media are well known and such use is not recommended. At present, consistent results have been documented using dynamic CT techniques only.

CONTRAINDICATIONS

Refer to PRECAUTIONS, General, concerning hypersensitivity. Conray should not be used for myelography. Arthrography should not be performed if infection is present in or near the joint. Percutaneous transhepatic cholangiography is contraindicated in patients with coagulation defects and prolonged prothrombin times. Endoscopic retrograde cholangiopancreatography is contraindicated during an acute attack of pancreatitis or during severe clinically evident cholangitis and in patients in whom endoscopy is prohibited.

WARNINGS

WARNINGS

SEVERE ADVERSE EVENTS - INADVERTENT INTRATHECAL ADMINISTRATION: Serious adverse reactions have been reported due to the inadvertent intrathecal administration of iodinated contrast media that are not indicated for intrathecal use. These serious adverse reactions include: death, convulsions, cerebral hemorrhage, coma, paralysis, arachnoiditis, acute renal failure, cardiac arrest, seizures, rhabdomyolysis, hyperthermia, and brain edema. Special attention must be given to ensure that this drug product is not administered intrathecally.

Ionic iodinated contrast media inhibit blood coagulation, in vitro, more than nonionic contrast media. Nonetheless, it is prudent to avoid prolonged contact of blood with syringes containing ionic contrast media.

Serious, rarely fatal, thromboembolic events causing myocardial infarction and stroke have been reported during angiographic procedures with both ionic and nonionic contrast media. Therefore, meticulous intravascular administration technique is necessary, particularly during angiographic procedures, to minimize thromboembolic events. Numerous factors, including length of procedure, catheter and syringe material, underlying disease state and concomitant medications may contribute to the development of thromboembolic events. For these reasons, meticulous angiographic techniques are recommended, including close attention to guidewire and catheter manipulation, use of manifold systems and/or three-way stopcocks, frequent catheter flushing with heparinized saline solutions and minimizing the length of the procedure. The use of plastic syringes in place of glass syringes has been reported to decrease, but not eliminate, the likelihood of in vitro clotting.

Serious or fatal reactions have been associated with the administration of iodine-containing radiopaque media. It is of utmost importance to be completely prepared to treat any contrast medium reaction.

Serious neurologic sequelae, including permanent paralysis, have been reported following cerebral arteriography, selective spinal arteriography and arteriography of vessels supplying the spinal cord. The intravascular injection of a contrast medium should never be made following the administration of vasopressors since they strongly potentiate neurologic effects.

In patients with subarachnoid hemorrhage, a rare association between contrast administration and clinical deterioration, including convulsions and death, has been reported. Therefore, administration of intravascular iodinated ionic contrast media in these patients should be undertaken with caution.

A definite risk exists in the use of intravascular contrast agents in patients who are known to have multiple myeloma. In such instances, anuria has developed, resulting in progressive uremia, renal failure and eventually death. Although neither the contrast agent nor dehydration has separately proved to be the cause of anuria in myeloma, it has been speculated that the combination of both may be causative factors. The risk in myelomatous patients is not a contraindication to the procedure; however, partial dehydration in the preparation of these patients for the examination is not recommended, since this may predispose to precipitation of myeloma protein in the renal tubules. No form of therapy, including dialysis, has been successful in reversing the effect. Myeloma, which occurs most commonly in persons over 40, should be considered before instituting intravascular administration of contrast agents.

Administration of radiopaque materials to patients known or suspected to have pheochromocytoma should be performed with extreme caution. If, in the opinion of the physician, the possible benefits of such procedures outweigh the considered risks, the procedures may be performed; however, the amount of radiopaque medium injected should be kept to an absolute minimum. The blood pressure should be assessed throughout the procedure, and measures for treatment of a hypertensive crisis should be available.

Contrast media have been shown to promote the phenomenon of sickling in individuals who are homozygous for sickle cell disease when the material is injected intravenously or intra-arterially.

Convulsions have occurred in patients with primary or metastatic cerebral lesions following the administration of iodine-containing radiopaque media for the contrast enhancement of CT brain images.

In patients with advanced renal disease, iodinated contrast media should be used with caution, and only when the need for the examination dictates, since excretion of the medium may be impaired. Patients with combined renal and hepatic disease, those with severe hypertension or congestive heart failure, and recent renal transplant recipients may present an additional risk.

Renal failure has been reported in patients with liver dysfunction who were given an oral cholecystographic agent followed by an intravascular iodinated radiopaque agent, and also in patients with occult renal disease, notably diabetics and hypertensives. In these classes of patients, there should be no fluid restriction and every attempt made to maintain normal hydration, prior to contrast medium administration, since dehydration is the single most important factor influencing further renal impairment.

Acute renal failure has been reported in diabetic patients with diabetic nephropathy and in susceptible non-diabetic patients (often elderly with pre-existing renal disease) following the administration of iodinated contrast agents. Therefore, careful consideration of the potential risks should be given before performing this radiographic procedure in these patients.

Caution should be exercised in performing contrast medium studies in patients with endotoxemia and/or those with elevated body temperatures.

Reports of thyroid storm occurring following the intravascular use of iodinated radiopaque agents in patients with hyperthyroidism or with an autonomously functioning thyroid nodule, suggest that this additional risk be evaluated in such patients before use of this drug. Iodine containing contrast agents may alter the results of thyroid function tests which depend on iodine estimation, e.g. PBI and radioactive iodine uptake studies. Such tests, if indicated, should be performed prior to the administration of this preparation.

Thyroid Dysfunction in Pediatric Patients 0 to 3 Years of Age:

Thyroid dysfunction characterized by hypothyroidism or transient thyroid suppression has been reported after both single exposure and multiple exposures to iodinated contrast media (ICM) in pediatric patients 0 to 3 years of age.

Younger age, very low birth weight, prematurity, underlying medical conditions affecting thyroid function, admission to neonatal or pediatric intensive care units, and congenital cardiac conditions are associated with an increased risk of hypothyroidism after ICM exposure. Pediatric patients with congenital cardiac conditions may be at the greatest risk given that they often require high doses of contrast during invasive cardiac procedures.

An underactive thyroid during early life may be harmful for cognitive and neurological development and may require thyroid hormone replacement therapy. After exposure to ICM, individualize thyroid function monitoring based on underlying risk factors, especially in term and preterm neonates.

Severe Cutaneous Adverse Reactions: Severe cutaneous adverse reactions (SCAR) may develop from 1 hour to several weeks after intravascular contrast agent administration. These reactions include Stevens-Johnson syndrome and toxic epidermal necrolysis (SJS/TEN), acute generalized exanthematous pustulosis (AGEP) and drug reaction with eosinophilia and systemic symptoms (DRESS). Reaction severity may increase and time to onset may decrease with repeat administration of contrast agent; prophylactic medications may not prevent or mitigate severe cutaneous adverse reactions. Avoid administering Conray to patients with a history of a severe cutaneous adverse reaction to Conray.

PRECAUTIONS

General

Diagnostic procedures which involve the use of iodinated intra-vascular contrast agents should be carried out under the direction of personnel skilled and experienced in the particular procedure to be performed. All procedures utilizing contrast media carry a definite risk of producing adverse reactions. While most reactions may be minor, life threatening and fatal reactions may occur without warning. The risk-benefit factor should always be carefully evaluated before such a procedure is undertaken. A fully equipped emergency cart, or equivalent supplies and equipment, and personnel competent in recognizing and treating adverse reactions of all severity, or situations which may arise as a result of the procedure, should be immediately available at all times. If a serious reaction should occur, immediately discontinue administration. Since severe delayed reactions have been known to occur, emergency facilities and competent personnel should be available for at least 30 to 60 minutes after administration (see ADVERSE REACTIONS).

Preparatory dehydration is dangerous and may contribute to acute renal failure in infants, young children, the elderly, patients with pre-existing renal insufficiency, patients with advanced vascular disease and diabetic patients.

Severe reactions to contrast media often resemble allergic responses. This has prompted the use of several provocative pretesting methods, none of which can be relied on to predict severe reactions. No conclusive relationship between severe reactions and antigen-antibody reactions or other manifestations of allergy has been established. The possibility of an idiosyncratic reaction in patients who have previously received a contrast medium without ill effect should always be considered. Prior to the injection of any contrast medium, the patient should be questioned to obtain a medical history with emphasis on allergy and hypersensitivity. A positive history of bronchial asthma or allergy, including food, a family history of allergy, or a previous reaction or hypersensitivity to a contrast agent, may imply a greater than usual risk. Such a history, by suggesting histamine sensitivity and consequently proneness to reactions, may be more accurate than pre-testing in predicting the potential for reaction, although not necessarily the severity or type of reaction in the individual case. A positive history of this type does not arbitrarily contraindicate the use of a contrast agent, when a diagnostic procedure is thought essential, but does call for caution (see ADVERSE REACTIONS).

Prophylactic therapy including corticosteroids and antihistamines should be considered for patients who present with a strong allergic history, a previous reaction to a contrast medium, or a positive pretest, since the incidence of reaction in these patients is two to three times that of the general population. Adequate doses of corticosteroids should be started early enough prior to contrast medium injection to be effective and should continue through the time of injection and for 24 hours after injection. Antihistamines should be administered within 30 minutes of the contrast medium injection. Recent reports indicate that such pre-treatment does not prevent serious life-threatening reactions, but may reduce both their incidence and severity. A separate syringe should be used for these injections.

General anesthesia may be indicated in the performance of some procedures in young or uncooperative children and in selected adult patients; however, a higher incidence of adverse reactions has been reported in these patients. This may be attributable to the inability of the patient to identify untoward symptoms, or to the hypotensive effect of anesthesia, which can prolong the circulation time and increase the duration of contact of the contrast agent.

Angiography should be avoided whenever possible in patients with homocystinuria because of the risk of inducing thrombosis and embolism.

Information for Patients

Patients receiving iodinated intravascular contrast agents should be instructed to:

1. Inform your physician if you are pregnant.
2. Inform your physician if you are diabetic or if you have multiple myeloma, pheochromocytoma, homozygous sickle cell disease or known thyroid disease (see WARNINGS).
3. Inform your physician if you are allergic to any drugs, food or if you had any reactions to previous injections of dyes used for x-ray procedures (see PRECAUTIONS, General).
4. Inform your physician about any other medications you are currently taking, including non-prescription drugs.
5. Consult with your physician if, at some future date, any thyroid tests are planned. The iodine in this agent may interfere with later thyroid tests.
6. Advise patients to inform their physician if they develop a rash after receiving Conray.
7. Advise parents/caregivers about the risk of developing thyroid dysfunction after Conray administration. Advise parents/caregivers about when to seek medical care for their child to monitor for thyroid dysfunction (see WARNINGS).

Carcinogenesis, Mutagenesis, Impairment of Fertility

No long-term animal studies have been performed to evaluate carcinogenic potential. However, animal studies suggest that this drug is not mutagenic and does not affect fertility in males or females.

Pregnancy Category B

Reproduction studies have been performed in mice, rats, and rabbits at doses up to 6.6 times the human dose and have revealed no evidence of impaired fertility or harm to the fetus due to Conray. There are, however, no adequate and well controlled studies in pregnant women. Because animal reproduction studies are not always predictive of human response, this drug should be used during pregnancy only if clearly needed.

Nursing Mothers

Iothalamate salts are excreted unchanged in human milk. Because of the potential for adverse effects in nursing infants, bottle feedings should be substituted for breast feedings for 24 hours following the administration of this drug.

(Precautions for specific procedures receive comment under that procedure.)

Pediatric Use

Thyroid function tests indicative of thyroid dysfunction, characterized by hypothyroidism or transient thyroid suppression have been uncommonly reported following iodinated contrast media administration in pediatric patients, including term and preterm neonates; some patients were treated for hypothyroidism. After exposure to iodinated contrast media, individualize thyroid function monitoring in pediatric patients 0 to 3 years of age based on underlying risk factors, especially in term and preterm neonates (see WARNINGS and ADVERSE REACTIONS).

ADVERSE REACTIONS

Adverse reactions to injectable contrast media fall into two categories: chemotoxic reactions and idiosyncratic reactions.

Chemotoxic reactions result from the physio-chemical properties of the contrast media, the dose and speed of injection. All hemodynamic disturbances and injuries to organs or vessels perfused by the contrast medium are included in this category.

Idiosyncratic reactions include all other reactions. They occur more frequently in patients 20 to 40 years old. Idiosyncratic reactions may or may not be dependent on the amount of dose injected, the speed of injection, the mode of injection and the radiographic procedure. Idiosyncratic reactions are subdivided into minor, intermediate and severe. The minor reactions are self-limited and of short duration; the severe reactions are life-threatening and treatment is urgent and mandatory.

Fatalities have been reported following the administration of iodine-containing contrast agents. Based upon clinical literature, the incidence of death is reported to range from one in 10,000 (0.01 percent) to less than one in 100,000 (0.001 percent).

The following adverse reactions have been observed in conjunction with the use of iodine-containing contrast agents.

The most frequent adverse reactions are nausea, vomiting, facial flush and a feeling of body warmth. These are usually of brief duration. Other reactions include the following:

Hypersensitivity reactions: Dermal manifestations of urticaria with or without pruritus, erythema and maculopapular rash. Dry mouth. Sweating. Conjunctival symptoms. Facial, peripheral and angioneurotic edema. Symptoms related to the respiratory system include sneezing, nasal stuffiness, coughing, choking, dyspnea, chest tightness and wheezing, which may be initial manifestations of more severe and infrequent reactions including asthmatic attack, laryngospasm and bronchospasm with or without edema, pulmonary edema, apnea and cyanosis. Rarely, these allergic-type reactions can progress into anaphylaxis with loss of consciousness and coma and severe cardiovascular disturbances.

Cardiovascular reactions: Generalized vasodilation, flushing and venospasm. Occasionally, thrombosis or rarely, thrombophlebitis. Red blood cell clumping and agglutination, crenation and interference in clot formation. Extremely rare cases of disseminated intravascular coagulation resulting in death have been reported. Severe cardiovascular responses include rare cases of hypotensive shock, coronary insufficiency, cardiac arrhythmia, fibrillation and arrest. These severe reactions are usually reversible with prompt and appropriate management; however, fatalities have occurred.

Endocrine reactions: Hyperthyroidism, hypothyroidism.

Skin and Subcutaneous Tissue Disorders: Reactions range from mild (e.g. rash, erythema, pruritus, urticaria and skin discoloration) to severe: [e.g. Stevens-Johnson syndrome and toxic epidermal necrolysis (SJS/TEN), acute generalized exanthematous pustulosis (AGEP) and drug reaction with eosinophilia and systemic symptoms (DRESS)].

Technique reactions: Extravasation with burning pain, hematomas, ecchymosis and tissue necrosis, paresthesia or numbness, vascular constriction due to injection rate, thrombosis and thrombophlebitis.

Neurological reactions: Spasm, convulsions, aphasia, syncope, paresis, paralysis resulting from spinal cord injury and pathology associated with syndrome of transverse myelitis, visual field losses which are usually transient but may be permanent, coma and death.

Other reactions: Headache, trembling, shaking, chills without fever and lightheadedness. Temporary renal shutdown or other nephropathy.

(Adverse reactions to specific procedures receive comment under that procedure.)

OVERDOSAGE

Overdosage may occur. The adverse effects of overdosage are life-threatening and affect mainly the pulmonary and cardiovascular system. The symptoms may include cyanosis, bradycardia, acidosis, pulmonary hemorrhage, convulsions, coma and cardiac arrest. Treatment of an overdose is directed toward the support of all vital functions and prompt institution of symptomatic therapy.

Iothalamate salts are dialyzable.

The intravenous LD50 value of various concentrations of Iothalamate Meglumine (in grams of iodine/kilogram body weight) varied from 5.7 to 8.9 g/kg in mice and 9.8 to 11.2 g/kg in rats. The LD50 values decrease as the rate of injection increases.

DOSAGE AND ADMINISTRATION

It is advisable that Conray be at or close to body temperature when injected.

The patient should be instructed to omit the meal that precedes the examination. Appropriate premedication, which may include a barbiturate, tranquilizer or analgesic drug, may be administered prior to the examination.

A preliminary film is recommended to check the position of the patient and the x-ray exposure factors.

If a minor reaction occurs during administration, the injection should be slowed or stopped until the reaction has subsided. If a major reaction occurs, the injection should be discontinued immediately.

Under no circumstances should either corticosteroids or antihistamines be mixed in the same syringe with the contrast medium because of a potential for chemical incompatibility.

Parenteral drug products should be inspected visually for particulate matter and discoloration prior to administration.

EXCRETORY UROGRAPHY

Following intravenous injection, Conray is rapidly excreted by the kidneys. Conray may be visualized in the renal parenchyma 30 seconds following bolus injection. Maximum radiographic density in the calyces and pelves occurs in most instances within 3 to 8 minutes after injection. In patients with severe renal impairment contrast visualization may be substantially delayed.

Patient Preparation

Appropriate preparation of the patient is important for optimal visualization. A low residue diet is recommended for the day preceding the examination and a laxative is given the evening before the examination, unless contraindicated.

Precautions

Infants and small children should not have any fluid restrictions prior to excretory urography. Injections of Conray represent an osmotic load which, if superimposed on increased serum osmolality due to partial dehydration, may magnify hypertonic dehydration (see WARNINGS and PRECAUTIONS, General concerning preparatory dehydration).

Adverse Reactions

See section on general Adverse Reactions.

Usual Dosage

Adults - The usual dose is 30 to 60 mL. Children 14 years of age and over, of average weight, may receive the adult dose. The total dose is normally injected within 30 to 90 seconds. Higher dosage may be indicated to achieve optimum results in instances where poor visualization may be anticipated (e.g., elderly patients or patients with impaired renal function). When nephrograms and/or sequential urograms are desired, the total dose should be rapidly injected, normally within 15 to 30 seconds.

The dosage for children is reduced in proportion to age and body weight. The following approximate schedule is recommended for infants and children, based on a dosage of about 0.5 mL/kg of body weight:

Under 6 months of age | 5 mL
6-12 months | 8 mL
1-2 years | 10 mL
2-5 years | 12 mL
5-8 years | 15 mL
8-12 years | 18 mL
12-14 years | 20-30 mL

CEREBRAL ANGIOGRAPHY

Conray may be used to visualize the cerebral vasculature by any of the accepted techniques.

Patient Preparation

Cerebral angiography is normally performed with local or general anesthesia (see PRECAUTIONS, General). Premedication may be employed as indicated.

A preliminary radiograph is usually made prior to injection of the contrast agent.

Precautions

In addition to the general precautions previously described, cerebral angiography should be performed with special caution in patients with advanced arteriosclerosis, severe hypertension, cardiac decompensation, senility, recent cerebral thrombosis or embolism, and migraine.

Adverse Reactions

The major sources of cerebral arteriographic adverse reactions appear to be related to repeated injections of the contrast material, administration of doses higher than those recommended, the presence of occlusive atherosclerotic vascular disease and the method and technique of injection.

Adverse reactions are normally mild and transient. A feeling of warmth in the face and neck is frequently experienced. Infrequently, a more severe burning discomfort is observed.

Serious neurological reactions that have been associated with cerebral angiography and not listed under the general Adverse Reactions include stroke, amnesia and respiratory difficulties.

Cardiovascular reactions that may occur with some frequency are bradycardia and decrease in systemic blood pressure. The blood pressure change is transient and usually requires no treatment.

Usual Dosage

The usual dosage employed varies with the site and method of injection and the age, condition and weight of the patient. In adults, carotid and vertebral angiography, by either the percutaneous needle or catheter methods, is usually performed with a single rapid injection of 6 to 10 mL. Additional injections are made as indicated. Retrograde brachial cerebral angiography, in adults, is usually performed with a single rapid injection of 35 to 50 mL into the right brachial artery. Other dosages may be employed depending upon the vessel injected and the procedure followed. The dose for children is reduced in approximate proportion to age and body weight.

PERIPHERAL ARTERIOGRAPHY AND VENOGRAPHY

Conray may be injected to visualize the arterial and venous peripheral circulation. Arteriograms of the upper and lower extremities may be obtained by any of the established techniques. Most frequently, a percutaneous injection is made into the brachial artery in the arm or the femoral artery in the leg. Venograms are obtained by injection into an appropriate vein in the upper and lower extremity.

Patient Preparation

The procedure is normally performed with local or general anesthesia (see PRECAUTIONS, General). Premedication may be employed as indicated.

A preliminary radiograph is usually made prior to the injection of the contrast agent.

Precautions

In addition to the general precautions previously described, moderate decreases in blood pressure occur frequently with intra-arterial (brachial) injections. This change is usually transient and requires no treatment; however, the blood pressure should be monitored for approximately ten minutes following injection. Special care is required when venography is performed in patients with suspected thrombosis, phlebitis, severe ischemic disease, local infection or a totally obstructed venous system. In the presence of venous stasis, vein irrigation with normal saline should be considered following the procedure. Venography is optimally performed with a more dilute solution such as Conray 43 (Iothalamate Meglumine Injection USP 43%).

Extreme caution during injection of the contrast agent is necessary to avoid extravasation and fluoroscopy is recommended. This is especially important in patients with severe arterial or venous disease.

Adverse Reactions

In addition to the general adverse reactions previously described, hemorrhage and thrombosis have occurred at the puncture site of the percutaneous injection. Brachial plexus injury has been reported following axillary artery injection. Thrombophlebitis, syncope and very rare cases of gangrene have been reported following venography.

Usual Dosage

Peripheral Arteriography: In adults a single rapid injection of 20 to 40 mL is normally sufficient to visualize the entire extremity. The dose for children is reduced in proportion to body weight. Venography: The usual dose for adults is a single rapid injection of 20 to 40 mL. The dose for children is reduced in proportion to body weight. Following the procedure, the venous system should be flushed with either 5% dextrose in water (D5W) or normal saline (Sodium Chloride Injection USP) or the contrast medium should be removed by leg massage and/or leg elevation.

ARTHROGRAPHY

Precautions

In addition to the general precautions previously described, strict aseptic technique is required to prevent the introduction of infection. Fluoroscopic control should be used to ensure proper introduction of the needle into the synovial space and prevent extracapsular injection. Aspiration of excessive synovial fluid will reduce the pain on injection and prevent the rapid dilution of the contrast agent. It is important that undue pressure not be exerted during the injection.

Adverse Reactions

In addition to the general adverse reactions previously described arthrography may induce joint pain or discomfort which is usually mild and transient but occasionally may be severe and persist for 24 to 48 hours following the procedure. Effusion requiring aspiration may occur in patients with rheumatoid arthritis.

Usual Dosage

Arthrography is usually performed under local anesthesia. The amount of contrast agent required is solely dependent on the size of the joint to be injected and the technique employed.

The following dosage schedule for normal adult joints should serve only as a guide since joints may require more or less contrast medium for optimal visualization. Dosage should be reduced for children in proportion to body weight.

Knee, hip | 5-15 mL
Shoulder, ankle | 5-10 mL
Other | 1-4 mL

Passive or active manipulation is used to disperse the medium throughout the joint space.

The lower volumes of contrast medium are usually employed for double contrast examinations. Following the injection of the contrast medium 50 to 100 cc of either filtered room air or carbon dioxide is introduced for examination of the knee and lesser volumes for other joints. The concomitant use of epinephrine 1:1000 will reduce the rate of contrast medium absorption as well as the production of synovial fluids and consequent dilution of the medium.

DIRECT CHOLANGIOGRAPHY

Precautions

In addition to the general precautions previously described, in the presence of acute pancreatitis, direct cholangiography, if necessary, should be employed with caution, injecting no more than 5 to 10 mL without undue pressure. Percutaneous transhepatic cholangiography should only be attempted when compatible blood for potential transfusions is in readiness and emergency surgical facilities are available. The patient should be carefully monitored for at least 24 hours to ensure prompt detection of bile leakage and hemorrhage. Appropriate premedication of the patient is recommended and drugs which are cholespastic, such as morphine, should be avoided. Respiratory movements should be controlled during introduction of the needle.

Adverse Reactions

Adverse reactions may often be attributed to injection pressure or excessive volume of the medium resulting in overdistention of the ducts and producing local pain.

Some of the medium may enter the pancreatic duct which may result in pancreatic irritation. Occasionally, nausea, vomiting, fever, and tachycardia have been observed. Pancholangitis resulting in liver abscess or septicemia has been reported.

In percutaneous transhepatic cholangiography, some discomfort is common, but severe pain is unusual. Complications of the procedure are often serious and have been reported in 4 to 6 percent of patients. These reactions have included bile leakage and biliary peritonitis, gall bladder perforation, internal bleeding (sometimes massive), blood-bile fistula resulting in septicemia involving gram-negative organisms, and tension pneumothorax from inadvertent puncture of the diaphragm or lung. Bile leakage is more likely to occur in patients with obstructions that cause unrelieved high biliary pressure.

Dosage and Administration

It is advisable that Conray be at or close to body temperature when injected. The injection is made slowly without undue pressure, taking the necessary precautions to avoid the introduction of bubbles.

Operative – The usual dose is 10 mL but as much as 25 mL may be needed depending upon the caliber of the ducts. If desired, the contrast agent may be diluted 1:1 with Sodium Chloride Injection USP using strict aseptic procedures. Following surgical exploration of the ductal system, repeat studies may be performed before closure of the abdomen, using the same dose as before.

Postoperative – Postoperatively, the ductal system may be examined by injection of the contrast agent through an in-place T-tube. These delayed cholangiograms are usually made from the fifth to the tenth postoperative day prior to removal of the T-tube. The usual dose is the same as for operative cholangiography.

Percutaneous Transhepatic Cholangiography – This procedure is recommended for carefully selected patients for the differential diagnosis of jaundice due to extrahepatic biliary obstruction or parenchymal disease. The procedure is only employed where oral or intravenous cholangiography and other procedures have failed to provide the necessary information. In obstructed cases, percutaneous transhepatic cholangiography is used to determine the cause and site of obstruction to help plan surgery. The technique may also be of value in avoiding laparotomy in poor risk jaundice patients since failure to enter a duct suggests hepatocellular disease. Careful attention to technique is essential for the success and safety of the procedure. The procedure is usually performed under local anesthesia following analgesic premedication.

Depending upon the caliber of the biliary tree, a dose of 20 to 40 mL is generally sufficient to opacify the entire ductal system. If desired, the contrast agent may be diluted 1:1 with Sodium Chloride injection USP using strict aseptic procedures.

As the needle is advanced or withdrawn, a bile duct may be located by frequent aspiration for bile or mucus. Before the dose is administered, as much bile as possible is aspirated. The injection may be repeated for exposures in different planes and repositioning of the patient, if necessary, should be done with care. If a duct is not readily located by aspiration, successive small doses of 1 to 2 mL of the medium are injected into the liver as the needle is gradually withdrawn, until a duct is visualized by x-ray.

If no duct can be located after 3 or 4 attempts, the procedure should be terminated. Inability to enter a duct by a person experienced in the technique is generally considered to be strongly suggestive of hepatocellular disease.

Endoscopic retrograde cholangiopancreatography (ERCP) is indicated in carefully selected patients with known or suspected pancreatic or biliary tract disease when other diagnostic procedures have failed to provide the necessary diagnostic information. Prior to the development of ERCP, x-ray examination of the pancreatic ducts could only be obtained at laparotomy.

Precautions

Endoscopic retrograde cholangiopancreatography should only be performed by personnel skilled and experienced with the procedure, and careful attention to technique is essential for the success and safety of the procedure. Fluoroscopy is mandatory during injection to prevent over distention of the duct systems.

Adverse Reactions

Adverse reactions that have occurred which are attributable to either the procedure or to Conray, include nausea, vomiting, fever, severe abdominal pain, duodenal wall intravasation, septicemia, pancreatitis and perforation of the common bile duct associated with pathology.

Dosage and Administration

The procedure is usually performed following pharyngeal anesthesia and analgesic or sedative premedication. Duodenal motility may be controlled in patients with active duodenal peristalsis with an appropriate antiperistaltic agent.

The contrast medium should be injected slowly under fluoroscopic control employing the minimal dose that is adequate to visualize the common bile duct, the pancreatic duct, or both duct systems. The dosage will vary greatly depending on the pathological findings and can range from 10 to 100 mL for visualization of the common bile duct; and from 2 to 10 mL for visualization of the pancreatic duct.

Following the procedure, the patient should be kept under close observation for 24 hours.

CONTRAST ENHANCEMENT OF COMPUTED TOMOGRAPHIC (CT) BRAIN IMAGING

Tumors

Conray may be useful to enhance the demonstration of the presence and extent of certain malignancies such as: gliomas including malignant gliomas, glioblastomas, astrocytomas, oligodendrogliomas and gangliomas; ependymomas; medulloblastomas; meningiomas; neuromas; pinealomas; pituitary adenomas; craniopharyngiomas; germinomas; and metastatic lesions.

The usefulness of contrast enhancement for the investigation of the retrobulbar space and in cases of low grade or infiltrative glioma has not been demonstrated.

In cases where lesions have calcified, there is less likelihood of enhancement. Following therapy, tumors may show decreased or no enhancement.

Non-Neoplastic Conditions

The use of Conray may be beneficial in the image enhancement of non-neoplastic lesions. General infarctions of recent onset may be better visualized with the contrast enhancement, while some infarctions are obscured if contrast media are used. The use of iodinated contrast media results in contrast enhancement in about 60% of cerebral infarctions studied from one to four weeks from the onset of symptoms.

Sites of active infection may also be enhanced following contrast medium administration.

Arteriovenous malformations and aneurysms will show contrast enhancement. In the case of these vascular lesions, the enhancement is probably dependent on the iodine content of the circulating blood pool.

The opacification of the inferior vermis following contrast medium administration has resulted in false positive diagnoses in a number of normal studies.

Patient Preparation

No special patient preparation is required for contrast enhancement of CT brain scanning. However, it is advisable to ensure that patients are well hydrated prior to examination.

Usual Dosage

The usual dosage in adults and children is 2 mL/kg (1 mL/lb) by intravenous administration, not to exceed a total dose of 150 mL. In most cases, scanning may be performed immediately after completion of administration; however, when fast scanning equipment (less than 1 minute) is used, consideration should be given to waiting approximately 5 minutes to allow for maximum contrast enhancement.

CRANIAL COMPUTERIZED ANGIOTOMOGRAPHY

Conray may be administered for cranial computerized angiotomography when necessary to visualize the cerebral vessels to detect cerebrovascular lesions and to evaluate the anatomical relationship between the cerebral blood vessels and other parenchymal or space occupying lesions.

Usual Dosage

Conray may be administered by intravenous bolus injection, or by bolus injection followed by rapid infusion.

For bolus injection, the usual dose in adults and children is 0.5 to 1.0 mL/kg at an injection rate of 2 mL/second with scanning begun immediately after administration. This dose may be repeated as necessary. The total dose per procedure should not exceed 200 mL, and in children the total dose is reduced in approximate proportion to age and body weight.

In adults, when the combination bolus and infusion technique is used, a 50 mL bolus injection followed by a rapid infusion of 150 mL may be given or a 100 mL bolus injection followed by a rapid infusion of 100 mL may be used. Scanning is begun immediately after the bolus administration. In children, the dose is reduced in approximate proportion to age and body weight.

CONTRAST ENHANCEMENT IN BODY COMPUTED TOMOGRAPHY^1

Conray may be administered when necessary to visualize vessels and organs in patients undergoing CT of the chest, abdomen and pelvis.

Patient Preparation

No special patient preparation is required for contrast enhancement in body CT. In patients undergoing abdominal or pelvic examination, opacification of the bowel may be valuable in scan interpretation.

Precautions

In addition to the general precautions previously described, it is advisable to ensure that patients are adequately hydrated prior to examination. Patient motion, including respiration, can markedly affect image quality, therefore, patient cooperation is essential. The use of an intravascular contrast medium can obscure tumors in patients undergoing CT evaluation of the liver resulting in a false negative diagnosis. Dynamic CT scanning is the procedure of choice for malignant tumor enhancement (see CLINICAL PHARMACOLOGY).

Usual Dosage

Conray may be administered by bolus injection, by rapid infusion or by a combination of both.

For vascular opacification, a bolus injection of 25 to 50 mL may be used, repeated as necessary. When prolonged arterial or venous phase enhancement is required and for the enhancement of specific lesions, a rapid infusion of 150 mL may be used. In some instances, a 100 to 150 mL infusion may be employed to define the area of interest followed by bolus injections of 20 to 50 mL to clarify selected scans.

Intravenous digital subtraction angiography (IV DSA) is a radiographic modality which allows dynamic imaging of the arterial system following intravenous injection of iodinated x-ray contrast media through the use of image intensification, enhancement of the iodine signal and digital processing of the image data. Temporal subtraction of the images obtained during the “first arterial pass” of the injected contrast medium injection yield images which are devoid of bone and soft tissue.

Areas that have been most frequently examined by intravenous DSA are the heart, including coronary by-pass grafts; the pulmonary arteries; the arteries of the brachiocephalic circulation; the aortic arch; the abdominal aorta and its major branches including the celiac, mesenterics and renal arteries; the iliac arteries; and the arteries of the extremities.

Patient Preparation

No special patient preparation is required for intravenous digital subtraction angiography. However, it is advisable to ensure that patients are well hydrated prior to examination.

Precautions

In addition to the general precautions previously described, the risks associated with IV DSA are those usually attendant with catheter procedures and include intramural injections, vessel dissection and tissue extravasation. Small test injections of contrast medium made under fluoroscopic observation to ensure the catheter tip is properly positioned, and in the case of peripheral placement that the vein is of adequate size, will reduce this potential.

Patient motion, including respiration and swallowing, can result in marked image degradation yielding non-diagnostic studies. Therefore, patient cooperation is essential.

Adverse Reactions

See section on general Adverse Reactions.

Usual Dosage

Conray may be injected either centrally, into the superior or inferior vena cava, or peripherally into an appropriate arm vein. For central injections, catheters may be introduced at the antecubital fossa into either the basilic or cephalic vein or at the leg into the femoral vein and advanced to the distal segment of the corresponding vena cava. For peripheral injections, the catheter is introduced at the antecubital fossa into the appropriate size arm vein. In order to reduce the potential for extravasation during peripheral injection, a catheter of approximately 20 cm in length should be employed.

Depending on the area to be imaged, the usual dose range is 20 to 40 mL. Injections may be repeated as necessary.

Central catheter injections are usually made with a power injector with an injection rate of between 10 and 30 mL/second. When making peripheral injections, rates of 12 to 20 mL/second should be used, depending on the size of the vein. Also, since contrast medium may remain in the arm vein for an extended period following injection, it may be advisable to flush the vein, immediately following injection with an appropriate volume (20 to 25 mL) of 5% Dextrose in water or normal saline.

Arterial digital subtraction angiography provides images similar in quality to conventional film-screen systems. The advantages of arterial DSA when compared to standard film angiography include: the use of less contrast medium; the use of lower concentrations for some procedures; a decreased need for selective arterial catheterization reducing the possibility of dislodging atheromatous plaques or significantly reducing the blood flow in the artery; and a shortened examination time. The limitations of arterial DSA include: reduced spatial resolution; limited field size; and the inability to conduct simultaneous biplane examinations.

Patient Preparation

No special patient preparation is required for arterial DSA. However, it is advisable to ensure that patients are well hydrated prior to examination.

Precautions

In addition to the general precautions described, the risks associated with arterial DSA are those usually attendant with catheter procedures. Following the procedure, gentle pressure hemostasis is required, followed by observation and immobilization of the limb for several hours to prevent hemorrhage from the site of arterial puncture.

Usual Dosage

The following dosage schedule for adults should serve only as a guide since the volume administered, the concentration selected and the flow rate will be determined by the resolution of the equipment being used. As a general rule, the volume used and the flow rates for arterial DSA are 50% or less than that used for conventional film arteriography. Diagnostic studies have been obtained using Conray undiluted (28.2% iodine), diluted 1:1 (14.1% iodine), and diluted 1:2 (9.4% iodine). Sodium Chloride Injection USP or Water for Injection USP may be used for dilution.

The following doses, equivalent in iodine content to undiluted Conray, have been used.

Carotid or vertebral arteries: | 3-8 mL
Aortic Arch: | 15-25 mL
Subclavian and brachial arteries: | 5-15 mL
Major branches of the aorta: | 5-20 mL
Lumbar aorta (bifurcation): | 10-25 mL

HOW SUPPLIED

Conray® Glass Vials/Bottles | NDC Number
25x30 mL vials | 0019-0953-23
25x50 mL vials | 0019-0953-05
12x100 mL bottles | 0019-0953-10
12x150 mL bottles | 0019-0953-50

Storage

Store below 30°C (86°F). Exposing this product to very cold temperatures may result in crystallization of the salt. If this occurs, the container should be brought to room temperature. Shake vigorously to assure complete dissolution of any crystals. The speed of dissolution may be increased by heating with circulating warm air. Before use, examine the product to assure that all solids are redissolved, and that the container and closure have not been damaged.

This preparation is sensitive to light and must be protected from strong daylight or direct exposure to the sun.

As with all contrast media, glass containers should be inspected prior to use to ensure that breakage or other damage has not occurred during shipping and handling. All containers should be inspected for closure integrity. Damaged containers should not be used.

Reference
^1 Young, S. W., Turner, R.J., Castellino, R. A.: “A strategy for the contrast enhancement of malignant tumors using dynamic computed tomography and intravascular pharmacokinetics,” Radiology, 137:137-147, October 1980.

Manufactured by:
Liebel-Flarsheim Company LLC
Raleigh, NC 27616
Made in USA

GBT 0953A223
Revised 02/2023

Package Label Principal Display Panel - 150mL Bottle

For Intravascular Use
Sterile Solution

Conray®

150mL
NDC 0019-0953-50

Iothalamate Meglumine Injection USP 60%
282 mg/mL Organically Bound Iodine

NOT FOR INTRATHECAL USE
Rx Only

Protect from light • Store below 30°C (86°F).
Each mL contains 600 mg iothalamate meglumine, 0.09 mg edetate calcium disodium as a stabilizer, and 0.125 mg monobasic sodium phosphate as a buffer.
Single dose container • Discard unused portion
Usual Dosage: See Package Insert.

10390419

Manufactured by:
Liebel-Flarsheim Company LLC
Raleigh, NC 27616Made in USA